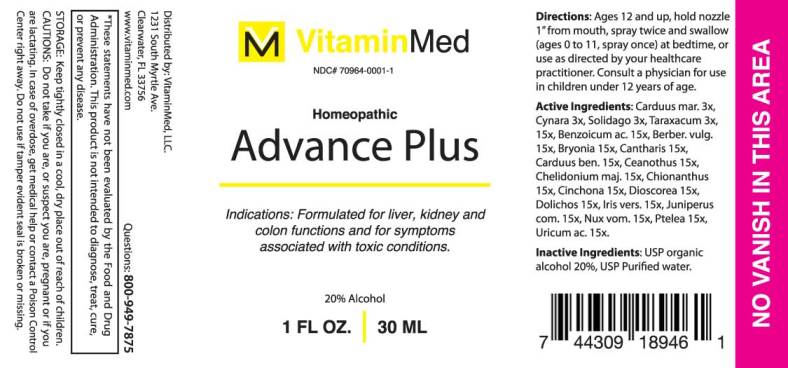 DRUG LABEL: Advance Plus
NDC: 70964-0001 | Form: SPRAY
Manufacturer: VitaminMed, LLC
Category: homeopathic | Type: HUMAN OTC DRUG LABEL
Date: 20190424

ACTIVE INGREDIENTS: MILK THISTLE 3 [hp_X]/1 mL; CYNARA SCOLYMUS LEAF 3 [hp_X]/1 mL; SOLIDAGO VIRGAUREA FLOWERING TOP 3 [hp_X]/1 mL; TARAXACUM OFFICINALE 3 [hp_X]/1 mL; BENZOIC ACID 15 [hp_X]/1 mL; BERBERIS VULGARIS ROOT BARK 15 [hp_X]/1 mL; BRYONIA ALBA ROOT 15 [hp_X]/1 mL; LYTTA VESICATORIA 15 [hp_X]/1 mL; CENTAUREA BENEDICTA 15 [hp_X]/1 mL; CEANOTHUS AMERICANUS LEAF 15 [hp_X]/1 mL; CHELIDONIUM MAJUS 15 [hp_X]/1 mL; CHIONANTHUS VIRGINICUS BARK 15 [hp_X]/1 mL; CINCHONA OFFICINALIS BARK 15 [hp_X]/1 mL; DIOSCOREA VILLOSA TUBER 15 [hp_X]/1 mL; MUCUNA PRURIENS FRUIT TRICHOME 15 [hp_X]/1 mL; IRIS VERSICOLOR ROOT 15 [hp_X]/1 mL; JUNIPER BERRY 15 [hp_X]/1 mL; STRYCHNOS NUX-VOMICA SEED 15 [hp_X]/1 mL; PTELEA TRIFOLIATA BARK 15 [hp_X]/1 mL; URIC ACID 15 [hp_X]/1 mL
INACTIVE INGREDIENTS: WATER; ALCOHOL

Drug Facts:

ACTIVE INGREDIENTS:

Carduus Marianus 3X, Cynara Scolymus 3X, Solidago Virgaurea 3X, Taraxacum Officinale 3X, 15X, Benzoicum Acidum 15X, Berberis Vulgaris 15X, Bryonia (Alba) 15X, Cantharis 15X, Carduus Benedictus 15X, Ceanothus Americanus 15X, Chelidonium Majus 15X, Chionanthus Virginica 15X, Cinchona Officinalis 15X, Dioscorea Villosa 15X, Dolichos Pruriens 15X, Iris Versicolor 15X, Juniperus Communis 15X, Nux Vomica 15X, Ptelea Trifoliata 15X, Uricum Acidum 15X.

INDICATIONS:

Formulated for liver, kidney and colon functions and for symptoms associated with toxic conditions.*

*These statements have not been evaluated by the Food and Drug Administration. This product is not intended to diagnose, treat, cure, or prevent any disease.

CAUTIONS:

Do not take if you are, or suspect you are, pregnant or if you are lactating.

In case of overdose, get medical help or contact a Poison Control Center right away.

Do not use if tamper evident seal is broken or missing.

STORAGE: Keep tightly closed in a cool, dry place out of reach of children.

KEEP OUT OF REACH OF CHILDREN:

Keep tightly closed in a cool, dry place out of reach of children.

In case of overdose, get medical help or contact a Poison Control Center right away.

DIRECTIONS:

Ages 12 and up, hold nozzle 1" from mouth, spray twice and swallow (ages 0 to 11, spray once) at bedtime, or use a directed by your healthcare practitioner. Consult a physician for use in children under 12 years of age.

INDICATIONS:

Formulated for liver, kidney and colon functions and for symptoms associated with toxic conditions.*

*These statements have not been evaluated by the Food and Drug Administration. This product is not intended to diagnose, treat, cure, or prevent any disease.

INACTIVE INGREDIENTS:

USP organic alcohol 20%, USP Purified water.

QUESTIONS:

Distributed by: VitaminMed, LLC.

1231 South Myrtle Ave.

Clearwater, FL 33756

www.vitaminmed.com Questions: 800-949-7875

PACKABE LABEL DISPLAY:

VitaminMed

NDC# 70964-0001-1

Homeopathic

Advance Plus

1 FL OZ. 30 ML